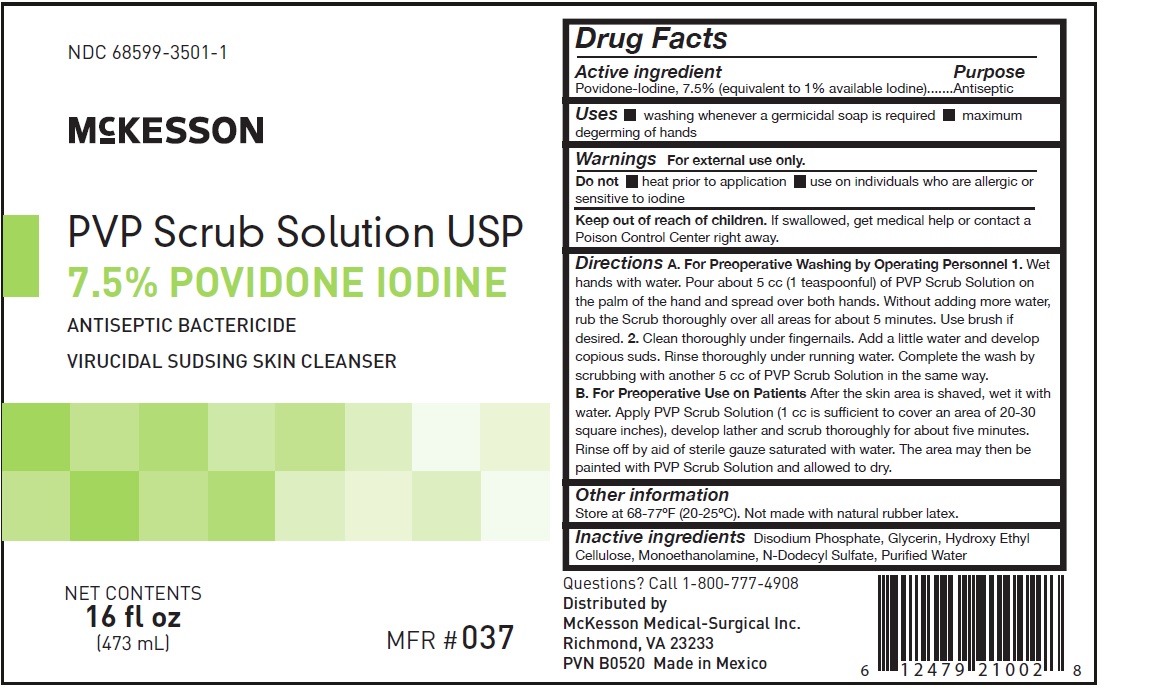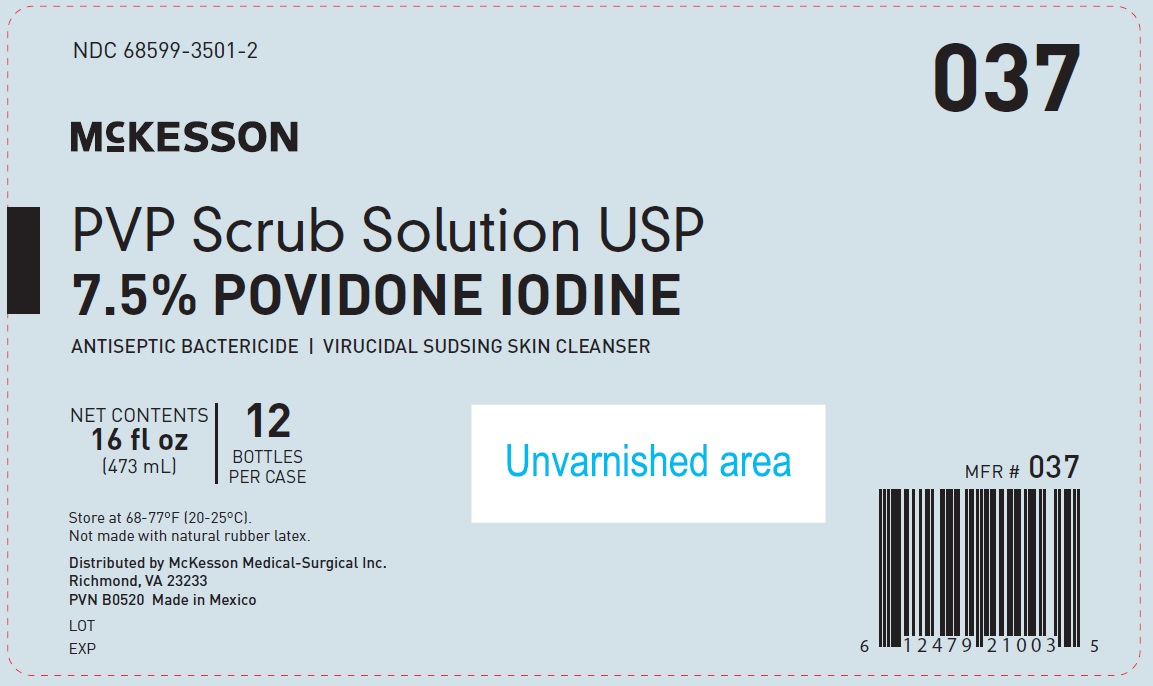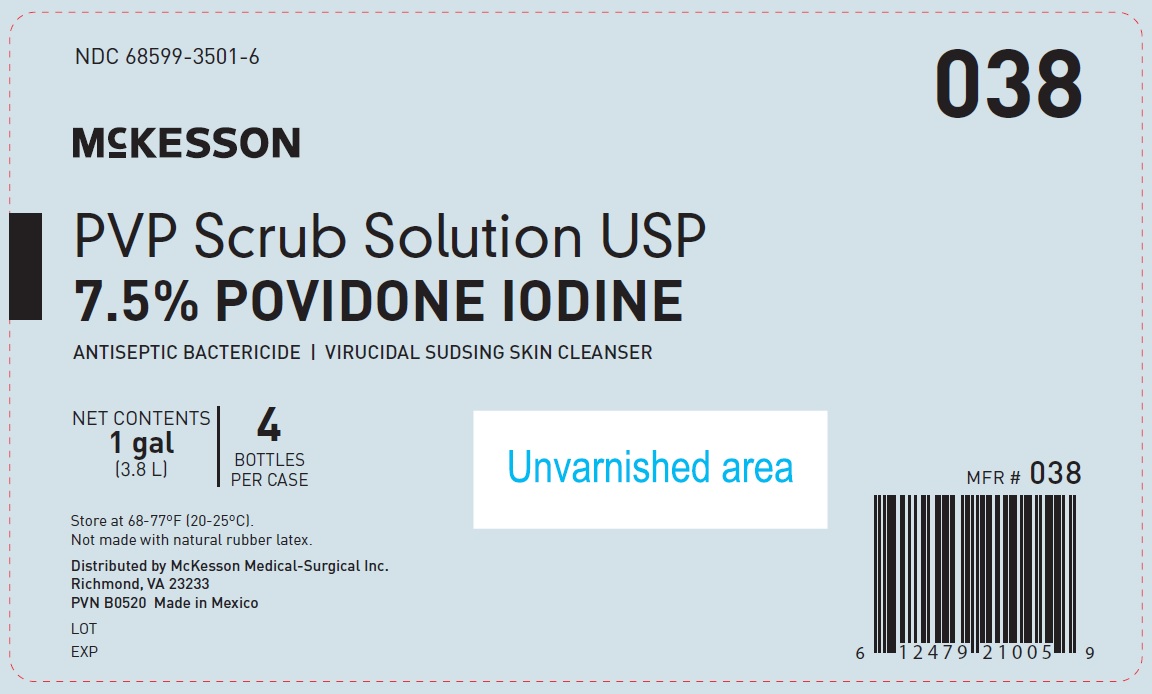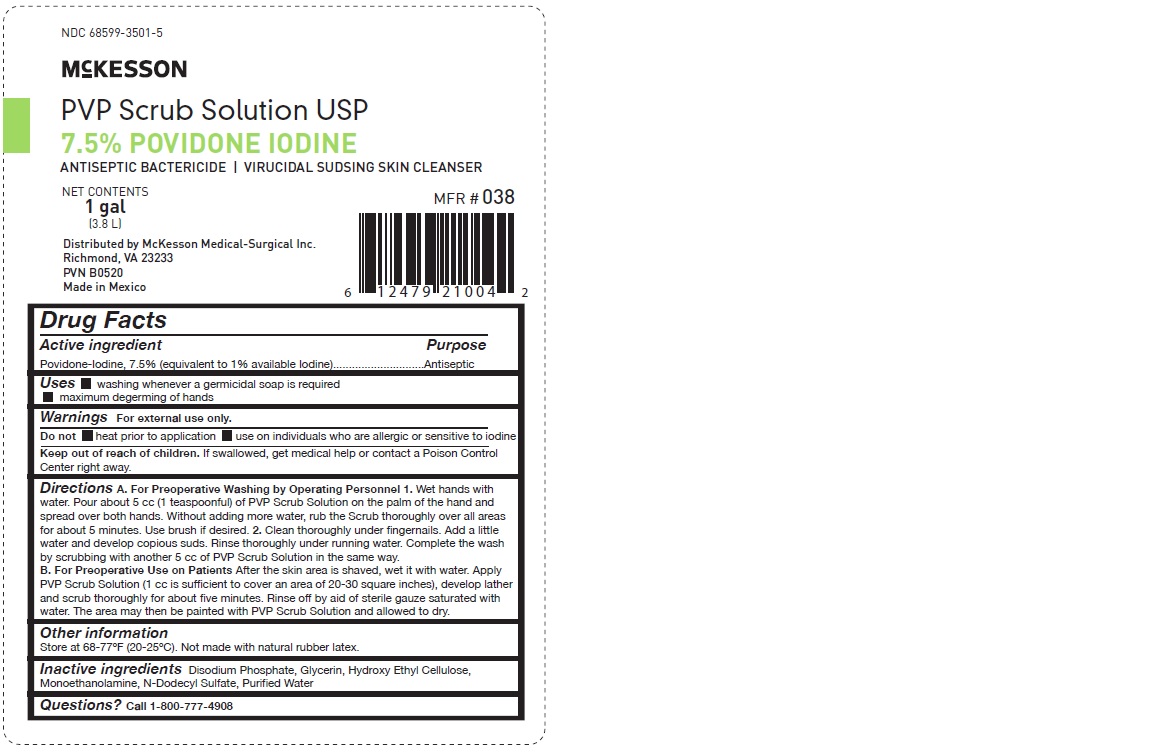 DRUG LABEL: PVP Scrub Solution
NDC: 68599-3501 | Form: SOLUTION
Manufacturer: McKesson Medical-Surgical Inc.
Category: otc | Type: HUMAN OTC DRUG LABEL
Date: 20241010

ACTIVE INGREDIENTS: POVIDONE-IODINE 7.5 mg/1 1
INACTIVE INGREDIENTS: HYDROXYETHYL CELLULOSE (5000 MPA.S AT 1%); GLYCERIN; MONOETHANOLAMINE; LAURYL SULFATE; WATER; SODIUM PHOSPHATE, DIBASIC, ANHYDROUS

PURPOSE

Antiseptic

WARNINGS

For external use only

Do not• heat prior to application • use on individuals who are allergic or sensitive to iodine

KEEP OUT OF REACH OF CHILDREN

Is swallowed, get medical help or contact a Poison Control Center right away

OTHER SAFETY INFORMATION

Do not store above 77°F (25ºC) - Do not store below 68°F (20°C)

Not made with natural rubber latex

INACTIVE INGREDIENT

Disodium Phosphate, Glycerin, Hydroxy Ethyl Cellulose, Monoethanolamine, N-Dodecyl Sulfate, Purified Water

ACTIVE INGREDIENT

Povidone-Iodine, 7.5% (equivalent to 1% available iodine)

INDICATIONS AND USAGE

-Washing whenever a germicidal soap is required

-Maximum degerming of hands

DOSAGE AND ADMINISTRATION

A. For Preoperative Washing by Operating Personnel

1. Wet hands with water. Pour about 5 cc (1 teaspoonful) of PVP Scrub Solution on the palm of the hand and spread over both hands. Without adding more water, rub the Scrub thoroughly over all areas for about five minutes. Use brush if desired.

2. Clean thoroughly under fingernails. Add a litle water and develop copious suds. Rinse thoroughly under running water. Complete the wash by scrubbing with another 5 cc of PVP Scrub Solution in the same way.

B. For Preoperative Use on Patients

After the skin area is shaved, wet it with water. Apply PVP Scrub Solution (1 cc is sufficient to cover an area of 20-30 square inches), develop lather and scrub thoroughly for about five minutes. Rinse off by aid of sterile gauze saturated with water. The area may then be painted with PVP Scrub Solution and allowed to dry.

PACKAGE LABEL

NDC# 68599-3501-1

NDC # 68599-3501-2

McKesson

PVP scrub Solution USP

7.5% Povidone Iodine

Antiseptic Bactericide / Virucidal Sudsing Skin Cleanser

Net Contents 16 fl oz (473 mL)

12 bottles per case

MFR# 037

PACKAGE LABEL

NDC # 68599-3501-5

NDC# 68599-3501-6

McKesson

PVP scrub Solution USP

7.5% Povidone Iodine

Antiseptic Bactericide / Virucidal Sudsing Skin Cleanser

Net Contents 1 gal (3.8 L)

4 bottles per case

MFR# 038